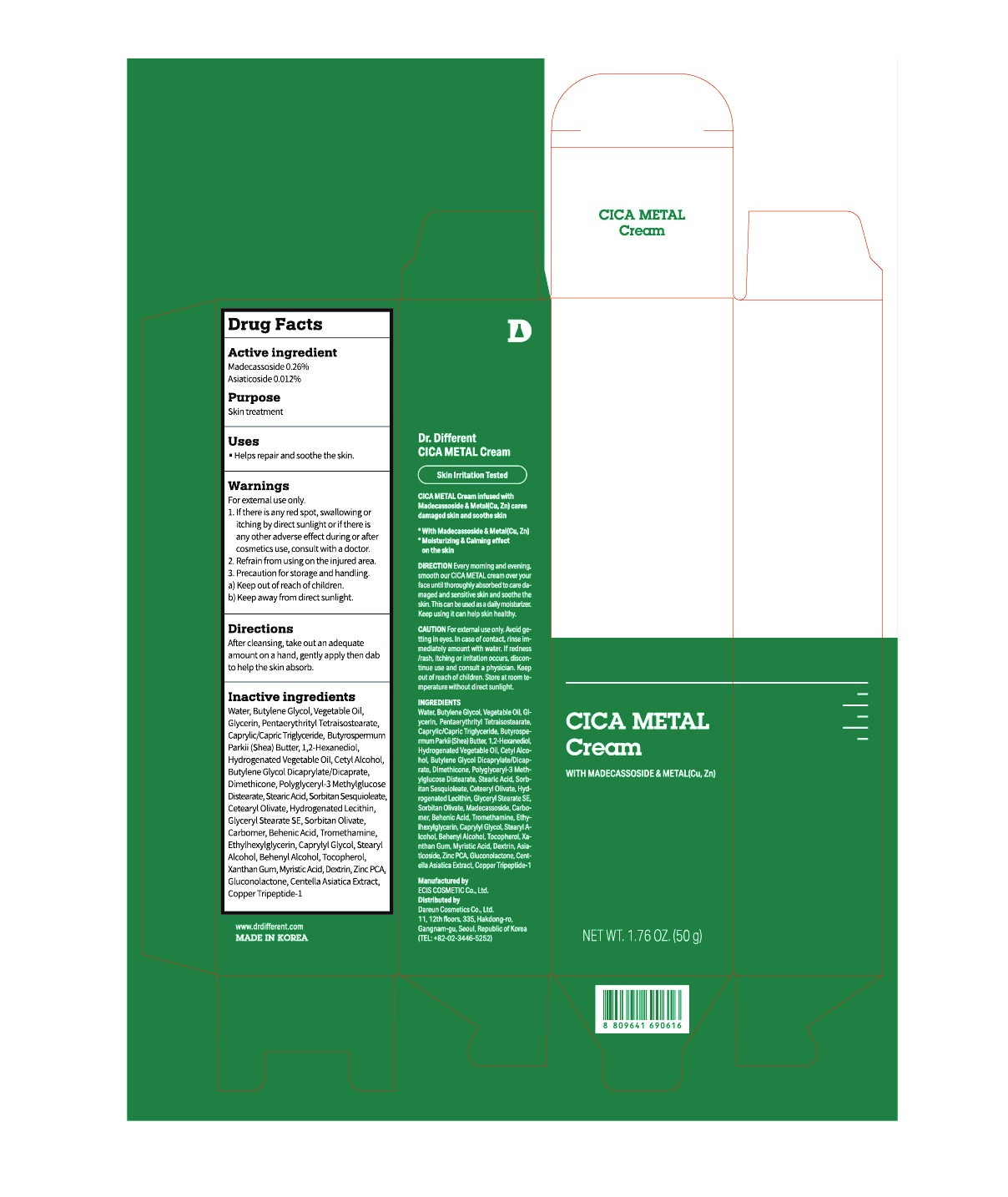 DRUG LABEL: Dr.Different CICA Metal
NDC: 81710-090 | Form: CREAM
Manufacturer: Dareun Cosmetics Co., Ltd.
Category: otc | Type: HUMAN OTC DRUG LABEL
Date: 20210803

ACTIVE INGREDIENTS: Madecassoside 0.26 g/100 g; Asiaticoside 0.012 g/100 g
INACTIVE INGREDIENTS: WATER; Butylene Glycol; Glycerin

ACTIVE INGREDIENTS

Madecassoside 0.26%
Asiaticoside 0.012%

INACTIVE INGREDIENTS

Water, Butylene Glycol, Vegetable Oil, Glycerin, Pentaerythrityl Tetraisostearate, Caprylic/Capric Triglyceride, Butyrospermum Parkii (Shea) Butter, 1,2-Hexanediol, Hydrogenated Vegetable Oil, Cetyl Alcohol, Butylene Glycol Dicaprylate/Dicaprate, Dimethicone, Polyglyceryl-3 Methylglucose Distearate, Stearic Acid, Sorbitan Sesquioleate, Cetearyl Olivate, Hydrogenated Lecithin, Glyceryl Stearate SE, Sorbitan Olivate, Carbomer, Behenic Acid, Tromethamine, Ethylhexylglycerin, Caprylyl Glycol, Stearyl Alcohol, Behenyl Alcohol, Tocopherol, Xanthan Gum, Myristic Acid, Dextrin, Zinc PCA, Gluconolactone, Centella Asiatica Extract, Copper Tripeptide-1

PURPOSE

Skin treatment

WARNINGS

For external use only.
1. If there is any red spot, swallowing or itching by direct sunlight or if there is any other adverse effect during or after cosmetics use, consult with a doctor.
2. Refrain from using on the injured area.
3. Precaution for storage and handling.
a) Keep out of reach of children.
b) Keep away from direct sunlight.

KEEP OUT OF REACH OF CHILDREN

Uses

■ Helps repair and soothe the skin.

Directions

After cleansing, take out an adequate amount on a hand, gently apply then dab to help the skin absorb.